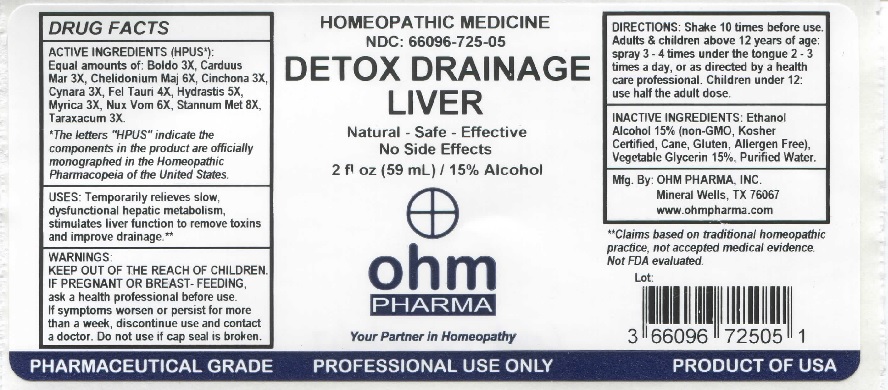 DRUG LABEL: Detox Drainage Liver
NDC: 66096-725 | Form: LIQUID
Manufacturer: OHM PHARMA INC.
Category: homeopathic | Type: HUMAN OTC DRUG LABEL
Date: 20211229

ACTIVE INGREDIENTS: PEUMUS BOLDUS LEAF 3 [hp_X]/59 mL; MILK THISTLE 3 [hp_X]/59 mL; CHELIDONIUM MAJUS 6 [hp_X]/59 mL; CINCHONA OFFICINALIS BARK 3 [hp_X]/59 mL; CYNARA SCOLYMUS LEAF 3 [hp_X]/59 mL; BOS TAURUS BILE 4 [hp_X]/59 mL; GOLDENSEAL 5 [hp_X]/59 mL; MORELLA CERIFERA ROOT BARK 3 [hp_X]/59 mL; STRYCHNOS NUX-VOMICA SEED 6 [hp_X]/59 mL; TIN 8 [hp_X]/59 mL; TARAXACUM OFFICINALE 3 [hp_X]/59 mL
INACTIVE INGREDIENTS: ALCOHOL; GLYCERIN; WATER

OHM Detox Drainage Liver

ACTIVE INGREDIENT

ACTIVE INGREDIENTS (HPUS*): Equal amounts of: Boldo 3X, Carduus Mar 3X, Chelidonium Maj 6X, Cinchona 3X, Cynara 3X, Fel Tauri 4X, Hydrastis 5X, Myrica 3X, Nux Vomica 6X, Stannum Met 8X, Taraxacum 3X.

*The letters "HPUS" indicate the components in the product are officially monographed in the Homeopathic Pharmacopeia of the United States.

INDICATIONS AND USAGE

USES: Temporarily relieves slow, dysfuntional hepatic metabolism, stimulates liver function to remove toxins and improve drainage.**

** This statement has not been evaluated by the FDA. It is based on documented Homeopathic Materia Medica.

WARNINGS

WARNINGS: IF PREGNANT OR BREAST-FEEDING, ask a health professional before use. If symptoms worsen or persist for more than a week, discontinue use and contact a doctor.

- KEEP OUT OF REACH OF CHILDREN.

DOSAGE AND ADMINISTRATION

DIRECTIONS: Shake 10 times before use. Adults & children above 12 years of age: spray 3-4 times under the tongue 2-3 times a day, or as directed by a health care professional. Children under 12 use half the adult dose.

Do not use if cap seal is broken

INACTIVE INGREDIENT

INACTIVE INGREDIENTS: Ethanol Alcohol 15% (Non-GMO, Kosher Certified, Cane, Gluten, Allergen Free), Vegetable Glycerin 15%, Purified Water.

QUESTIONS

Mfg. By: OHM PHARMA, INC. Mineral Wells TX 76067. www.ohmpharma.com

PACKAGE LABEL

HOMEOPATHIC MEDICINE

NDC: 66096-725-05

DETOX DRAINAGE LIVER

Natural - Safe - Effective

No Side Effects

2 fl oz (59mL) / 15% Alcohol

PRODUCT OF USA

PURPOSE

Temporarily relieves slow, dysfuntional hepatic metabolism.